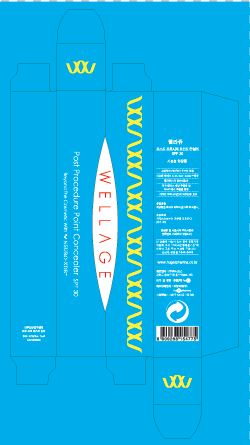 DRUG LABEL: WELLAGE Post Procedure Point Concealer
NDC: 69346-4001 | Form: CREAM
Manufacturer: HUGEL PHARMA CO.,LTD
Category: otc | Type: HUMAN OTC DRUG LABEL
Date: 20150102

ACTIVE INGREDIENTS: TITANIUM DIOXIDE 25 g/100 g
INACTIVE INGREDIENTS: WATER; DIMETHICONE; GLYCERIN

Drug Facts

ACTIVE INGREDIENT

titanium dioxide

INACTIVE INGREDIENT

isopropyl myristate, mica candelilla wax, sorbitan olivate ceresin, dimethicone, lanolin, methicone, etc

PURPOSE

sun block, skin protectant

keep out of reach of the children

INDICATIONS AND USAGE

apply proper amount to the skin

WARNINGS

・Stop using the product when you have skin problems or the product disagrees with your skin
・Stop using the product immediately and consult a dermatologist if you have redness, swelling, itching or irritation on the skin while or after using the product.
・If the product gets into the eyes, don't rub but rinse with water.
・Don't place the product in any place where it will be subjected to extremely high or low temperatures or direct sunlight.

DOSAGE AND ADMINISTRATION

for external use only